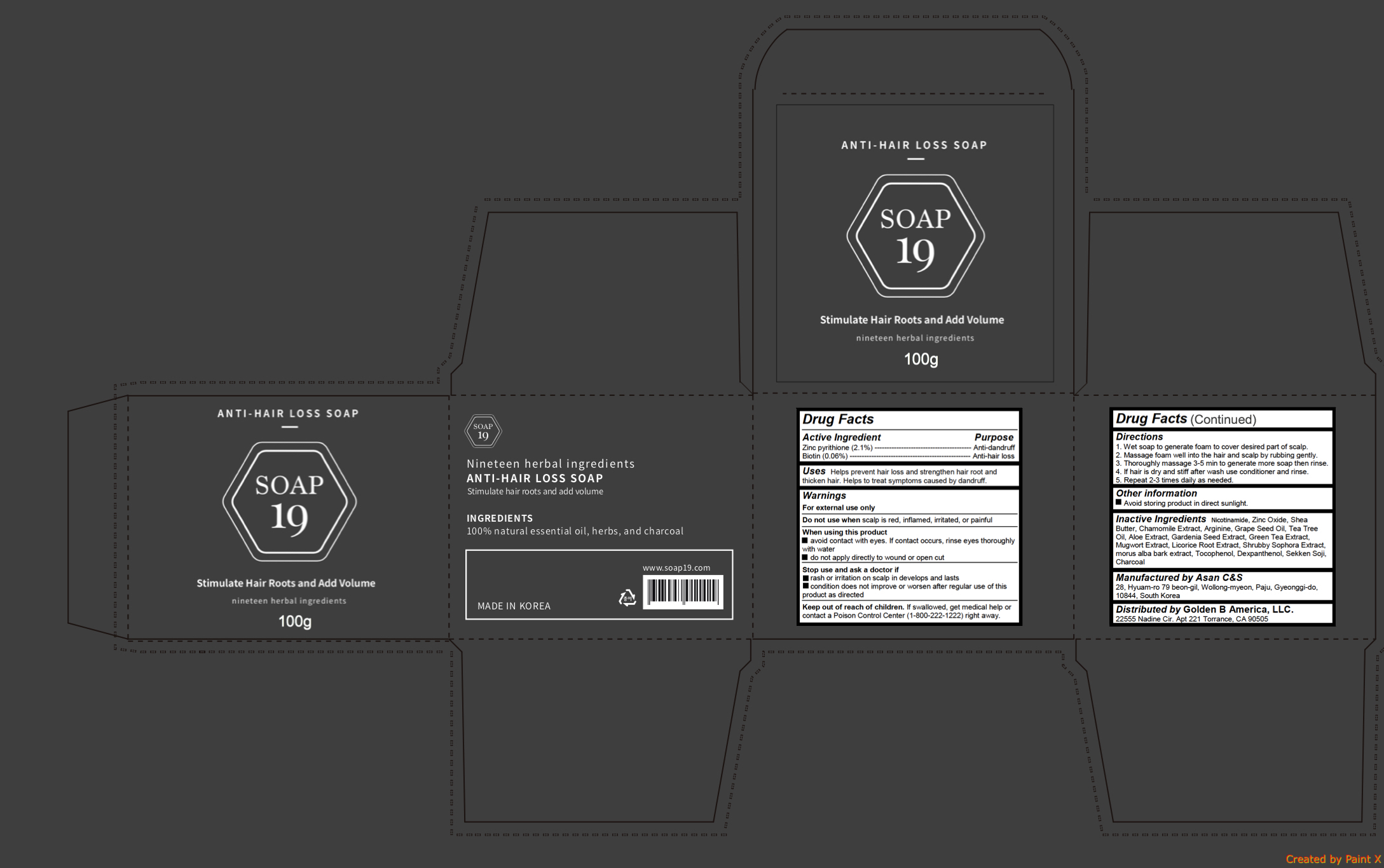 DRUG LABEL: Anti Hair Loss
NDC: 72100-100 | Form: SOAP
Manufacturer: Golden B America, LLC.
Category: otc | Type: HUMAN OTC DRUG LABEL
Date: 20180301

ACTIVE INGREDIENTS: PYRITHIONE ZINC 2.1 g/100 g; BIOTIN 0.06 g/100 g
INACTIVE INGREDIENTS: SHEA BUTTER; CHAMOMILE; ARGININE; NIACINAMIDE; ZINC OXIDE; GRAPE SEED OIL; TEA TREE OIL; ALOE; GREEN TEA LEAF; ARTEMISIA PRINCEPS LEAF; LICORICE; MORUS ALBA BARK; TOCOPHEROL; DEXPANTHENOL; ACTIVATED CHARCOAL

Anti Hair Loss Soap

Active ingredients

Zinc pyrithione (2.1%)

Biotin (0.06%)

Purpose

Anti-dandruff

Anti-hairloss

Uses

Helps prevent hair loss and strengthen hair root and thicken hair. Helps to treat symptoms caused by dandruff

Warnings

For external use only

Do not use when scalp is red, inflamed, irritated, or painful

When using this product

- avoid contact with eyes. If contact occurs, rinse eyes thoroughly with water
- do not apply directly to wound or open cut

Stop use and ask a doctor if

- rash or irritation on scalp in develops and lasts
- condition does not improve or worsen after regular use of this product as directed

Keep out of reach of children. If swallowed, get medical help or contact a Poison Control Center (1-800-222-1222) right away.

Directions

1. Wet soap to generate foam to cover desired part of scalp.

2. Massage foam well into the hair and scalp by rubbing gently.

3. Thoroughly massage 3-5 min to generate more soap then rinse.

4. If hair is dry and stiff after wash use conditioner and rinse.

5. Repeat 2-3 times daily as needed.

Keep out of reach of children. If swallowed, get medical help or contact a Poison Control Center (1-800-222-1222) right away.

Inactive ingredients

Nicotinamide, Zinc Oxide, Shea Butter, Chamomile Extract, Arginine, Grape Seed Oil, Tea Tree Oil, Aloe Extract, Gardenia Seed Extract, Green Tea Extract, Mugwort Extract, Licorice Root Extract, Shrubby Sophora Extract, morus alba bark extract, Tocophenol, Dexpanthenol, Sekken Soji, Charcoal